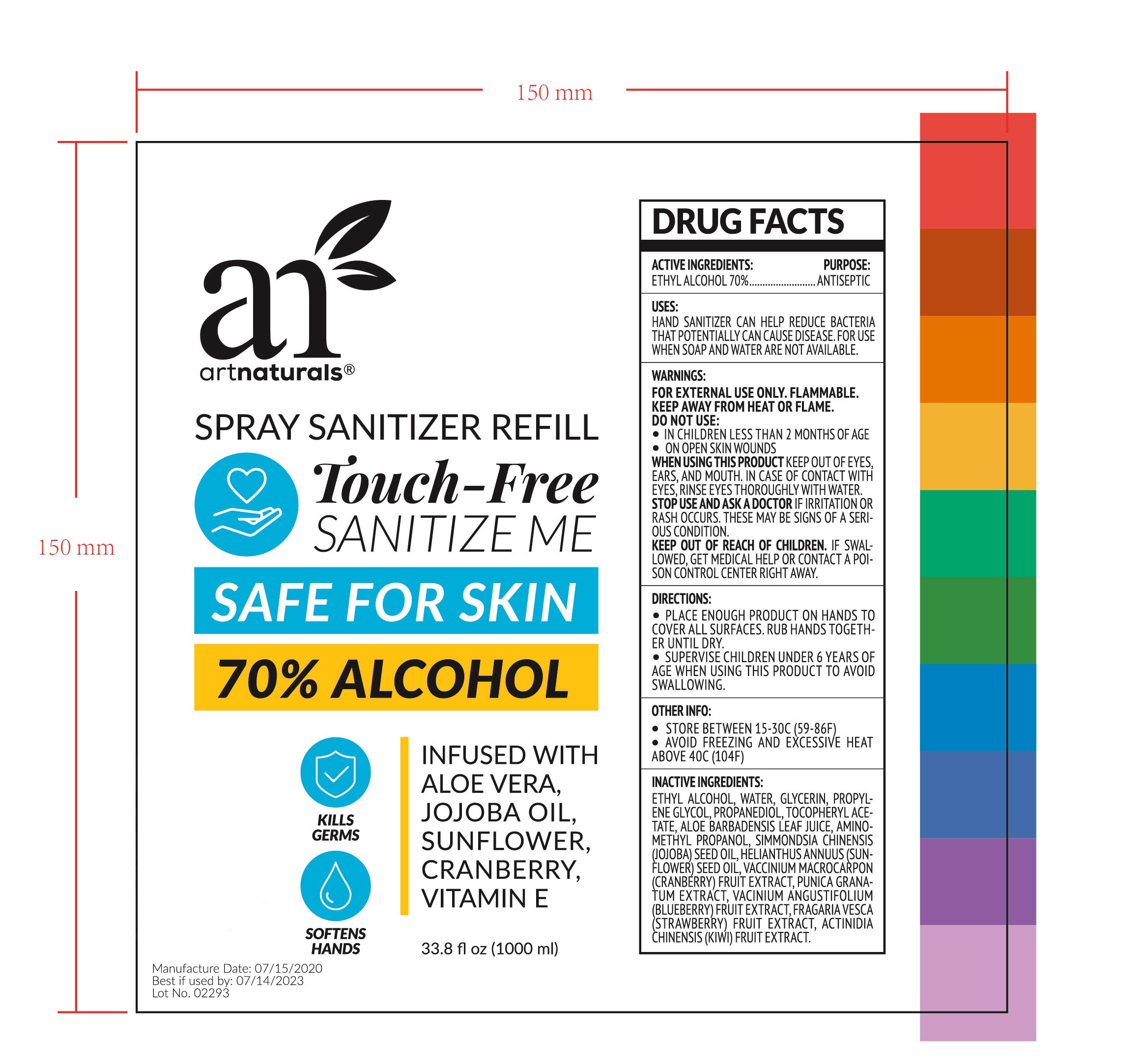 DRUG LABEL: HAND SANITIZER
NDC: 47993-296 | Form: GEL
Manufacturer: NINGBO JIANGBEI OCEAN STAR TRADING CO.,LTD
Category: otc | Type: HUMAN OTC DRUG LABEL
Date: 20201105

ACTIVE INGREDIENTS: ALCOHOL 70 g/112 mL
INACTIVE INGREDIENTS: WATER; GLYCERIN; PROPYLENE GLYCOL; PROPANEDIOL; .ALPHA.-TOCOPHEROL ACETATE; ALOE VERA LEAF; AMINOMETHYLPROPANOL; JOJOBA OIL; SUNFLOWER OIL; CRANBERRY JUICE; PUNICA GRANATUM LEAF; VACCINIUM ANGUSTIFOLIUM LEAF; FRAGARIA VESCA LEAF; KIWI FRUIT

47993-296

Active ingredients

Ethyl Alcohol 70%

PURPOSE

Antiseptic

Uses：

Hand sanitizer can help reduce bacteria that potentially can cause disease. For use when soap and water are not available.

Warnings:

For external use only. Flammable.

Keep away from heat or flame.

Do not use：

- In children less than 2 months of age.
- On open skin wounds.

When using this product keep out of eyes, ears, and mouth. In case of contact with eyes, rinse eyes thoroughly with water.

Stop use and ask a doctor if irritation or rash occurs. These may be signs of a serious condition.

Keep out of reach of children. If swallowed, get medical help or contact a Poison Control Center right away.

Directions:

- Place enough product on hands to cover all surfaces. Rub hands together until dry.
- Surpervise children under 6 years of age when using this product to avoid swallowing.

Other info:

- Store between 15-30℃（59-86℉）
- Avoid freezing and excessive heat above 40℃（104℉）

Inactive Ingredients:

Ethyl Alcohol, Water, Glycerin, Propylene glycol, Propanediol, Tocopheryl acetate, Aloe barbadensis leaf juice, Aminomethyl propanol, Simmondsia chinensis (jojoba) seed oil, Helianthus annuus (sunflower) seed oil, Vaccinium macrocarpon (cranberry) fruit extract, Punica granatum extract, Vaccinium angustifolium (blueberry) fruit extract, Fragaria chiloensis (strawberry) fruit extract, Actinidia chinesis (kiwi) fruit extract.